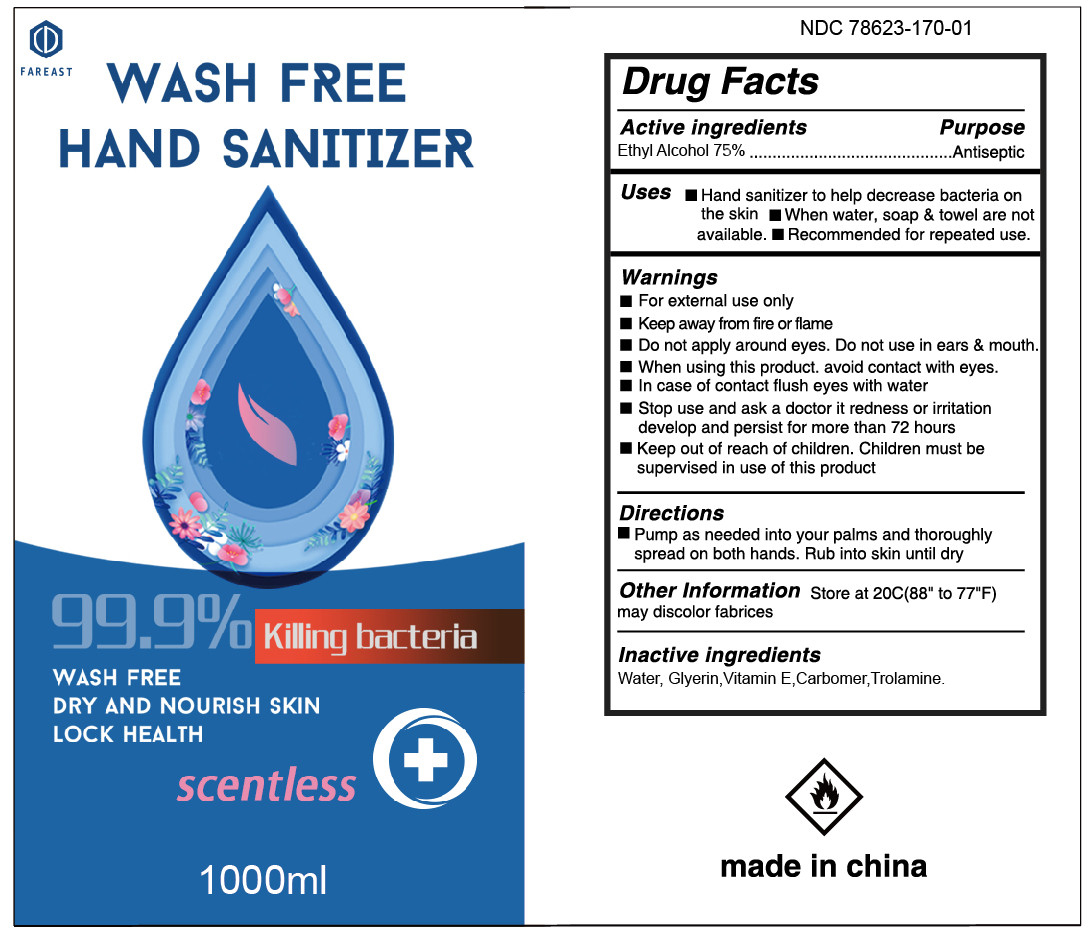 DRUG LABEL: Hand Sanitizer
NDC: 78623-275 | Form: GEL
Manufacturer: ningbo fareast industry co.,ltd
Category: otc | Type: HUMAN OTC DRUG LABEL
Date: 20210111

ACTIVE INGREDIENTS: ALCOHOL 75 mL/100 mL
INACTIVE INGREDIENTS: WATER

ACTIVE INGREDIENT

alcohol 75%v/v purpose : antibacterial

INDICATIONS AND USAGE

to help reduce bacteria that potentially can cause disease.for use when soap and water are not available

WARNINGS

for external use only,flammable,keep away from heat or flame

DO NOT USE

in children less than 2 months of age
.on open skin wounds

when using this product keep out of eyes,ears,and mouth in case of contact with eyes,rinse eyes thorough with water
stop use and ask a doctor if irritation or rash occurs,these may be signs of a serious condition.
keep out of reach of children,if swallowed,get medical help or contact a poison control center right away.

stop use and ask a doctor if irriation or rash occurs,these may be signs of a serious condition

keep out of reach of children ,if swallowed, get medical help or contact a posion control center right away .

DOSAGE AND ADMINISTRATION

place enough product on hands to cover all surface,rub hands together until dry
supervise children under 6 years when using this product to avoid swallowing

PACKAGE LABEL

1000ml NDC 78623-275-01